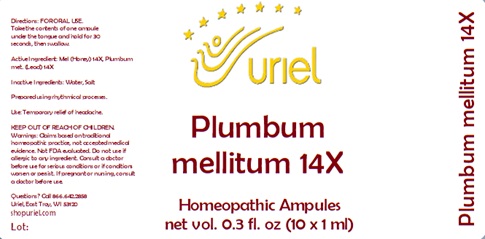 DRUG LABEL: Plumbum mellitum 14
NDC: 48951-8320 | Form: LIQUID
Manufacturer: Uriel Pharmacy Inc.
Category: homeopathic | Type: HUMAN OTC DRUG LABEL
Date: 20241025

ACTIVE INGREDIENTS: HONEY 14 [hp_X]/1 mL; LEAD 14 [hp_X]/1 mL
INACTIVE INGREDIENTS: SODIUM CHLORIDE; WATER

Plumbum mellitum 14

INDICATIONS AND USAGE

Directions: FOR ORAL USE.

DOSAGE AND ADMINISTRATION

Take the contents of one ampule under the tongue and hold for 30 seconds, then swallow.

Active Ingredient: Mel (Honey) 14X, Plumbum met. (Lead) 14X

Inactive Ingredients: Water, Salt

Prepared using rhythmical processes

PURPOSE

Use: Temporary relief of headache.

KEEP OUT OF REACH OF CHILDREN.

WARNINGS

Warnings: Claims based on traditional homeopathic practice, not accepted medical evidence. Not FDA evaluated. Do not use if allergic to any ingredient. Consult a doctor before use for serious conditions or if conditions worsen or persist. If pregnant or nursing, consult a doctor before use.

Questions? Call 866.642.2858
Uriel, East Troy, WI 53120
shopuriel.com Lot: